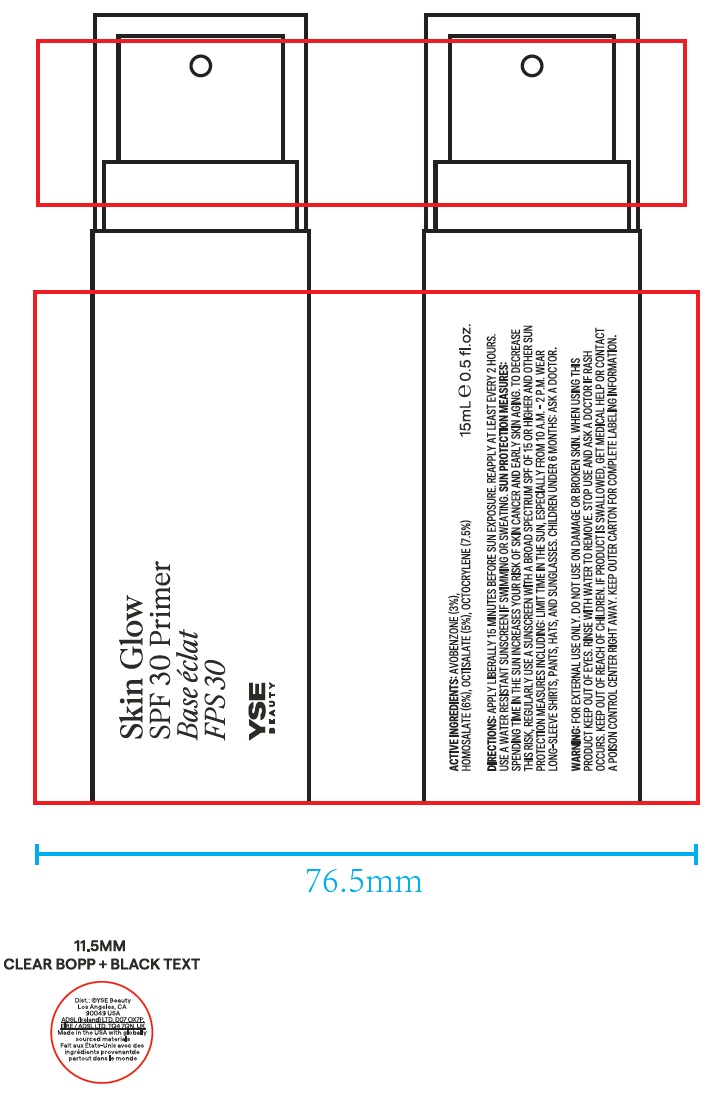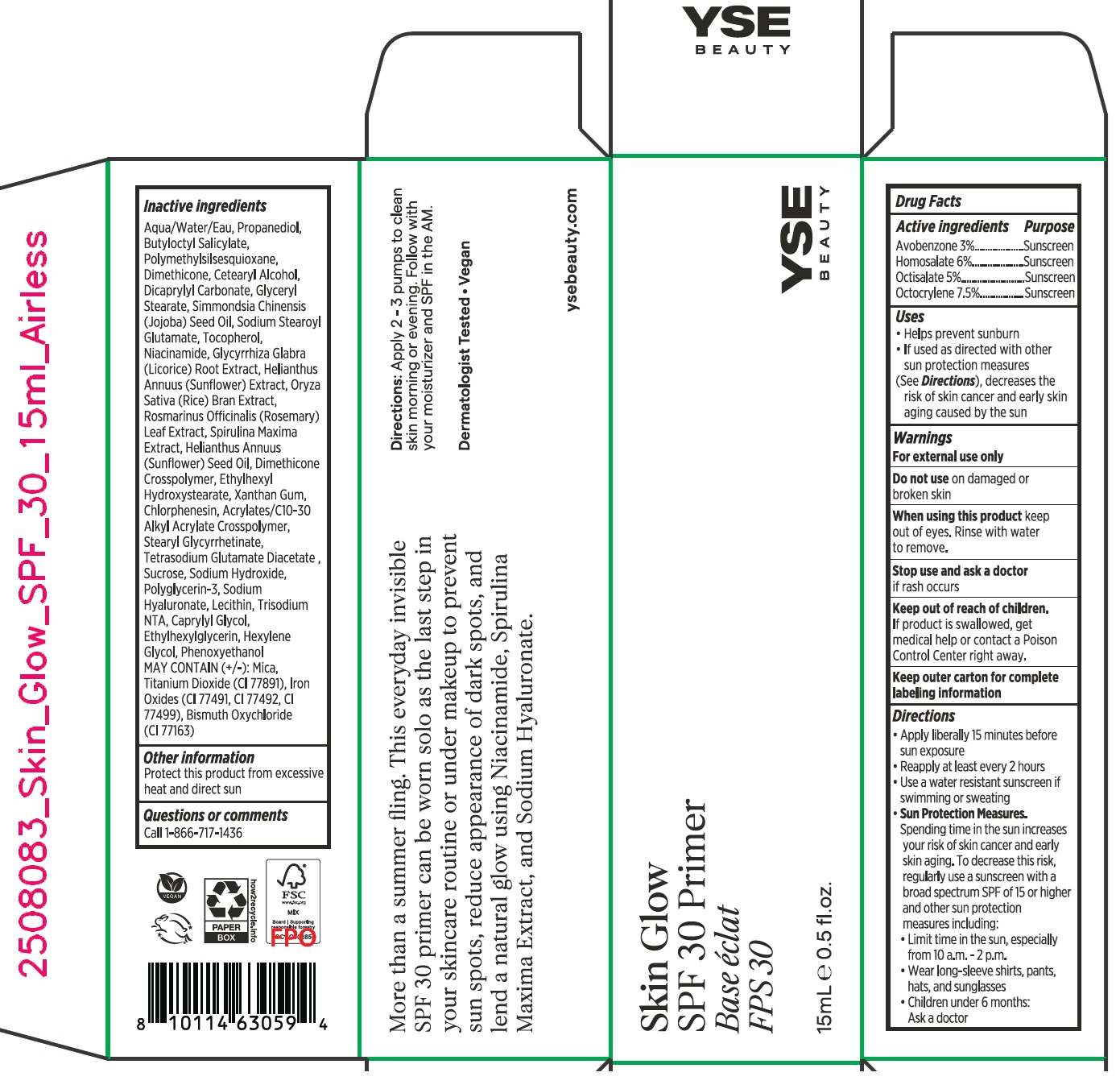 DRUG LABEL: YSE Beauty Skin Glow Primer SPF 30
NDC: 84075-001 | Form: CREAM
Manufacturer: MSS Beauty LLC
Category: otc | Type: HUMAN OTC DRUG LABEL
Date: 20251211

ACTIVE INGREDIENTS: AVOBENZONE 30 mg/1 mL; HOMOSALATE 60 mg/1 mL; OCTISALATE 50 mg/1 mL; OCTOCRYLENE 75 mg/1 mL
INACTIVE INGREDIENTS: WATER; PROPANEDIOL; BUTYLOCTYL SALICYLATE; CETEARYL ALCOHOL; DIMETHICONE; DICAPRYLYL CARBONATE; BISMUTH OXYCHLORIDE; GLYCERYL STEARATE; SODIUM STEAROYL GLUTAMATE; PHENOXYETHANOL; DIMETHICONE CROSSPOLYMER (450000 MPA.S); MICA; ETHYLHEXYL HYDROXYSTEARATE; XANTHAN GUM; FERRIC OXIDE RED; FERRIC OXIDE YELLOW; FERROSOFERRIC OXIDE; HELIANTHUS ANNUUS FLOWERING TOP; RICE BRAN; CHLORPHENESIN; CAPRYLYL GLYCOL; NIACINAMIDE; TITANIUM DIOXIDE; ETHYLHEXYLGLYCERIN; HEXYLENE GLYCOL; STEARYL GLYCYRRHETINATE; TETRASODIUM GLUTAMATE DIACETATE; SUCROSE; GLYCYRRHIZA GLABRA (LICORICE) ROOT POWDER; SODIUM HYDROXIDE; POLYGLYCERIN-3; TOCOPHEROL; ROSEMARY; ARTHROSPIRA MAXIMA; SODIUM HYALURONATE; ACRYLATES/C10-30 ALKYL ACRYLATE CROSSPOLYMER (60000 MPA.S); HELIANTHUS ANNUUS SEED WAX; LECITHIN, SOYBEAN; JOJOBA OIL, RANDOMIZED

YSE Beauty Skin Glow Primer SPF 30

Active ingredients

Avobenzone 3%

Homosalate 6%

Octisalate 5%

Octocrylene 7.5%

Purpose

Sunscreen

Uses

• Helps prevent sunburn

• If used as directed with other sun protection measures (See Directions), decreases the risk of skin cancer and early skin aging caused by the sun

Warnings

For external use only

Do not use

on damaged or broken skin

When using this product

keep out of eyes. Rinse with water to remove.

Stop use and ask a doctor

if rash occurs

Keep out of reach of children.

If product is swallowed, get medical help or contact a Poison Control Center right away.

Keep outer carton for complete labeling information

Directions

• Apply liberally 15 minutes before sun exposure
• Reapply at least every 2 hours
• Use a water resistant sunscreen if swimming or sweating
• Sun Protection Measures.
Spending time in the sun increases your risk of skin cancer and early skin aging. To decrease this risk, regularly use a sunscreen with a
broad spectrum SPF of 15 or higher and other sun protection measures including:
• Limit time in the sun, especially from 10 a.m. - 2 p.m.
• Wear long-sleeve shirts, pants, hats, and sunglasses
• Children under 6 months: Ask a doctor

Inactive ingredients

Water (Aqua), Propanediol, Butyloctyl Salicylate, Cetearyl Alcohol, Polymethylsilsesquioxane, Dimethicone, Dicaprylyl Carbonate, Bismuth Oxychloride (Cl 77163), Glyceryl Stearate, Jojoba Esters, Sodium Stearoyl Glutamate, Phenoxyethanol, Dimethicone Crosspolymer, Mica, Ethylhexyl Hydroxystearate, Xanthan Gum, Iron oxides (CI 77491,CI 77492, 77499), Helianthus Annus (Sunflower) Seed Wax, Oryza Sativa (Rice)Bran Extract, Chlorphenesin, Acrylates/C10-30 Alkyl Acrylate Crosspolymer, Caprylyl Glycol,Niacinamide, Titanium Dioxide (CI 77891), Ethylhexylglycerin, Hexylene Glycol, Stearyl Glycyrrhetinate, Tetrasodium Glutamate Diacetate, Helianthus Annuus (Sunflower) Extract, Sucrose, Glycyrrhiza Glabra (Licorice)Root Extract, Sodium Hydroxide, Polyglycerin-3, Tocopherol, Rosmarinus Officinalis (Rosemary) Leaf Extract, Spirulina Maxima Extract, Sodium Hyaluronate, Lecithin.

Other information

Protect this product from excessive heat and direct sun

Questions or comments

call 1-866-717-1436